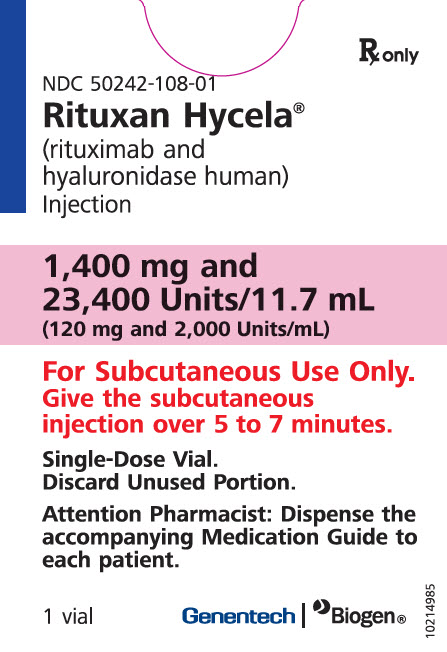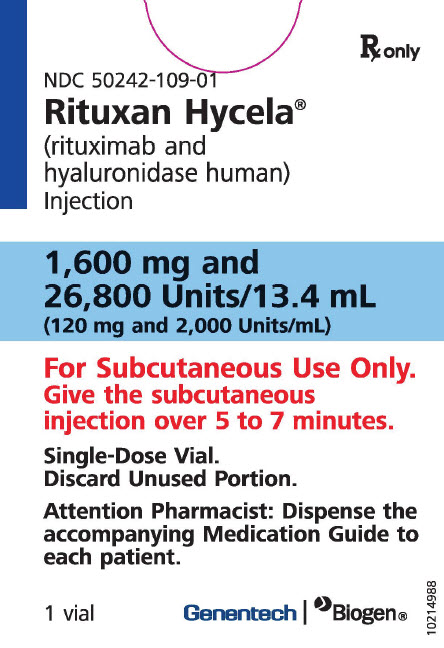 DRUG LABEL: Rituxan Hycela
NDC: 50242-108 | Form: INJECTION, SOLUTION
Manufacturer: Genentech, Inc.
Category: prescription | Type: HUMAN PRESCRIPTION DRUG LABEL
Date: 20251215

ACTIVE INGREDIENTS: RITUXIMAB 120 mg/1 mL; HYALURONIDASE (HUMAN RECOMBINANT) 2000 U/1 mL
INACTIVE INGREDIENTS: HISTIDINE; HISTIDINE HYDROCHLORIDE MONOHYDRATE; TREHALOSE DIHYDRATE; METHIONINE; POLYSORBATE 80; WATER

HIGHLIGHTS OF PRESCRIBING INFORMATION

These highlights do not include all the information needed to use RITUXAN HYCELA safely and effectively. See full prescribing information for RITUXAN HYCELA.
RITUXAN HYCELA® (rituximab and hyaluronidase human) injection, for subcutaneous use
Initial U.S. Approval: 2017

WARNING: SEVERE MUCOCUTANEOUS REACTIONS, HEPATITIS B VIRUS REACTIVATION and PROGRESSIVE MULTIFOCAL LEUKOENCEPHALOPATHY

See full prescribing information for complete boxed warning.

- Severe mucocutaneous reactions, some with fatal outcomes (5.1).
- Hepatitis B virus reactivation, in some cases resulting in fulminant hepatitis, hepatic failure, and death (5.2).
- Progressive multifocal leukoencephalopathy resulting in death (5.3).

RECENT MAJOR CHANGES

Dosage and Administration, Preparation and Administration (2.6) | 06/2021

1 INDICATIONS AND USAGE

RITUXAN HYCELA is a combination of rituximab, a CD20-directed cytolytic antibody, and hyaluronidase human, an endoglycosidase, indicated for the treatment of adult patients with:

- Follicular Lymphoma (FL) (1.1)
  - Relapsed or refractory, follicular lymphoma as a single agent
  - Previously untreated follicular lymphoma in combination with first line chemotherapy and, in patients achieving a complete or partial response to rituximab in combination with chemotherapy, as single-agent maintenance therapy
  - Non-progressing (including stable disease), follicular lymphoma as a single agent after first-line cyclophosphamide, vincristine, and prednisone (CVP) chemotherapy
- Diffuse Large B-cell Lymphoma (DLBCL) (1.2)
  - Previously untreated diffuse large B-cell lymphoma in combination with cyclophosphamide, doxorubicin, vincristine, prednisone (CHOP) or other anthracycline-based chemotherapy regimens
- Chronic Lymphocytic Leukemia (CLL) (1.3)
  - Previously untreated and previously treated CLL in combination with fludarabine and cyclophosphamide (FC)

Limitations of Use:

- Initiate treatment with RITUXAN HYCELA only after patients have received at least one full dose of a rituximab product by intravenous infusion. (1.4, 2.1, 5.4).
- RITUXAN HYCELA is not indicated for the treatment of non-malignant conditions. (1.4)

2 DOSAGE AND ADMINISTRATION

- For subcutaneous use only (2.1)
- All patients must receive at least one full dose of a rituximab product by intravenous infusion before receiving RITUXAN HYCELA by subcutaneous injection (2.1).
- FL/DLBCL: Administer 1,400 mg/23,400 Units (1,400 mg rituximab and 23,400 Units hyaluronidase human) subcutaneously according to recommended schedule (2.2, 2.3).
- CLL: Administer 1,600 mg/26,800 Units (1,600 mg rituximab and 26,800 Units hyaluronidase human) subcutaneously according to recommended schedule (2.4).
- Premedicate with acetaminophen and antihistamine before each dose; in addition, consider premedication with glucocorticoids (2.5, 5.4)
- Administer specified volume into subcutaneous tissue of abdomen: (2.6)
  - 11.7 mL from 1,400 mg/23,400 Units vial over approximately 5 minutes.
  - 13.4 mL from 1,600 mg/26,800 Units vial over approximately 7 minutes.
  - Observe 15 minutes following administration

3 DOSAGE FORMS AND STRENGTHS

Injection: (3)

- 1,400 mg rituximab and 23,400 Units hyaluronidase human per 11.7 mL (120 mg/2,000 Units per mL) solution in a single-dose vial
- 1,600 mg rituximab and 26,800 Units hyaluronidase human per 13.4 mL (120 mg/2,000 Units per mL) solution in a single-dose vial

4 CONTRAINDICATIONS

None.

5 WARNINGS AND PRECAUTIONS

- Hypersensitivity and other administration reactions: Local cutaneous reactions may occur more than 24 hours after administration. Interrupt injection if severe reaction develops. Premedicate before injection. (5.4)
- Tumor lysis syndrome: Administer aggressive intravenous hydration, anti hyperuricemic agents, monitor renal function. (5.5)
- Infections: Withhold and institute appropriate anti-infective therapy. (5.6)
- Cardiac adverse reactions: Discontinue in case of serious or life-threatening events. (5.7)
- Renal toxicity: Discontinue in patients with rising serum creatinine or oliguria. (5.8)
- Bowel obstruction and perforation: Consider and evaluate for abdominal pain, vomiting, or related symptoms. (5.9)
- Immunizations: Live virus vaccinations prior to or during treatment not recommended. (5.10)
- Embryo-Fetal toxicity: Can cause fetal harm. Advise females of reproductive potential of the potential risk to a fetus and use of effective contraception. (5.11)

6 ADVERSE REACTIONS

Most common adverse reactions (incidence of ≥ 20%) are: (6.1)

- FL: infections, neutropenia, nausea, constipation, cough, and fatigue
- DLBCL: infections, neutropenia, alopecia, nausea, and anemia
- CLL: infections, neutropenia, nausea, thrombocytopenia, pyrexia, vomiting, and injection site erythema

To report SUSPECTED ADVERSE REACTIONS, contact Genentech at 1-888-835-2555 or FDA at 1-800-FDA-1088 or www.fda.gov/medwatch.

DRUG INTERACTIONS

Renal toxicity when used in combination with cisplatin. (5.8)

8 USE IN SPECIFIC POPULATIONS

- Lactation: Advise not to breastfeed. (8.2)

FULL PRESCRIBING INFORMATION

WARNING: SEVERE MUCOCUTANEOUS REACTIONS, HEPATITIS B VIRUS REACTIVATION and PROGRESSIVE MULTIFOCAL LEUKOENCEPHALOPATHY

Severe Mucocutaneous Reactions

Severe, including fatal, mucocutaneous reactions can occur in patients receiving rituximab-containing products, including RITUXAN HYCELA [see Warnings and Precautions (5.1)].

Hepatitis B Virus (HBV) Reactivation

HBV reactivation can occur in patients treated with rituximab-containing products, including RITUXAN HYCELA, in some cases resulting in fulminant hepatitis, hepatic failure, and death. Screen all patients for HBV infection before treatment initiation, and monitor patients during and after treatment with RITUXAN HYCELA. Discontinue RITUXAN HYCELA and concomitant medications in the event of HBV reactivation [see Warnings and Precautions (5.2)].

Progressive Multifocal Leukoencephalopathy (PML), including fatal PML, can occur in patients receiving rituximab-containing products, including RITUXAN HYCELA [see Warnings and Precautions (5.3) and Adverse Reactions (6.1)].

1 INDICATIONS AND USAGE

1.1 Follicular Lymphoma (FL)

RITUXAN HYCELA is indicated for the treatment of adult patients with:

- Relapsed or refractory, follicular lymphoma as a single agent.
- Previously untreated follicular lymphoma in combination with first line chemotherapy and, in patients achieving a complete or partial response to rituximab in combination with chemotherapy, as single-agent maintenance therapy.
- Non-progressing (including stable disease), follicular lymphoma as a single agent after first-line cyclophosphamide, vincristine, and prednisone (CVP) chemotherapy.

1.2 Diffuse Large B-Cell Lymphoma (DLBCL)

RITUXAN HYCELA is indicated for the treatment of adult patients with previously untreated diffuse large B-cell lymphoma in combination with cyclophosphamide, doxorubicin, vincristine, prednisone (CHOP) or other anthracycline-based chemotherapy regimens.

1.3 Chronic Lymphocytic Leukemia (CLL)

RITUXAN HYCELA is indicated, in combination with fludarabine and cyclophosphamide (FC), for the treatment of adult patients with previously untreated and previously treated CLL.

1.4 Limitations of Use

- Initiate treatment with RITUXAN HYCELA only after patients have received at least one full dose of a rituximab product by intravenous infusion [see Dosage and Administration (2.1) and Warnings and Precautions (5.4)].
- RITUXAN HYCELA is not indicated for the treatment of non-malignant conditions.

2 DOSAGE AND ADMINISTRATION

2.1 Important Dosing Information

RITUXAN HYCELA is for subcutaneous use only. RITUXAN HYCELA should only be administered by a healthcare professional with appropriate medical support to manage severe reactions that can be fatal if they occur.

All patients must first receive at least one full dose of a rituximab product by intravenous infusion without experiencing severe adverse reactions before starting treatment with RITUXAN HYCELA. If patients are not able to receive one full dose by intravenous infusion, they should continue subsequent cycles with a rituximab product by intravenous infusion and not switch to RITUXAN HYCELA until a full intravenous dose is successfully administered [see Warnings and Precautions (5.4)].

Refer to the prescribing information for a rituximab product for intravenous infusion for additional information.

Premedicate before each dose of RITUXAN HYCELA [see Dosage and Administration (2.5)].

Dose reductions of RITUXAN HYCELA are not recommended. When RITUXAN HYCELA is given in combination with chemotherapy dose, reduce the chemotherapeutic drugs to manage adverse reactions.

2.2 Recommended Dosage for Follicular Lymphoma (FL)

All patients must receive at least one full dose of a rituximab product by intravenous infusion before starting treatment with RITUXAN HYCELA [see Dosage and Administration (2.1) and Warnings and Precautions (5.4)]. Premedicate before each dose [see Dosage and Administration (2.5)].

The recommended dose is RITUXAN HYCELA 1,400 mg/23,400 Units (1,400 mg rituximab and 23,400 Units hyaluronidase human) subcutaneously at a fixed dose irrespective of patient's body surface area according to the following schedules:

- Relapsed or Refractory, Follicular Lymphoma
  Administer once weekly for 3 or 7 weeks following a full dose of a rituximab product by intravenous infusion at week 1 (i.e., 4 or 8 weeks in total).
- Retreatment for Relapsed or Refractory, Follicular Lymphoma
  Administer once weekly for 3 weeks following a full dose of a rituximab product by intravenous infusion at week 1 (i.e., 4 weeks in total).
- Previously Untreated, Follicular Lymphoma
  Administer on Day 1 of Cycles 2–8 of chemotherapy (every 21 days), for up to 7 cycles following a full dose of a rituximab product by intravenous infusion on Day 1 of Cycle 1 of chemotherapy (i.e., up to 8 cycles in total). In patients with complete or partial response, initiate RITUXAN HYCELA maintenance treatment 8 weeks following completion of RITUXAN HYCELA in combination with chemotherapy. Administer RITUXAN HYCELA as a single-agent every 8 weeks for 12 doses.
- Non-progressing, Follicular Lymphoma after first line CVP chemotherapy
  Following completion of 6–8 cycles of CVP chemotherapy and a full dose of a rituximab product by intravenous infusion at week 1, administer once weekly for 3 weeks (i.e., 4 weeks in total) at 6 month intervals to a maximum of 16 doses.

2.3 Recommended Dosage for Diffuse Large B-Cell Lymphoma (DLBCL)

All patients must receive at least one full dose of a rituximab product by intravenous infusion in combination with CHOP chemotherapy before starting treatment with RITUXAN HYCELA [see Dosage and Administration (2.1) and Warnings and Precautions (5.4)]. Premedicate before each dose [see Dosage and Administration (2.5)].

The recommended dose for DLBCL is RITUXAN HYCELA 1,400 mg/23,400 Units (1,400 mg rituximab and 23,400 Units hyaluronidase human) at a fixed dose irrespective of patient's body surface area in combination with CHOP chemotherapy. Administer RITUXAN HYCELA 1,400 mg/23,400 Units on Day 1 of Cycles 2–8 of CHOP chemotherapy for up to 7 cycles following a full dose of a rituximab product by intravenous infusion at Day 1, Cycle 1 of CHOP chemotherapy (i.e., up to 6–8 cycles in total).

2.4 Recommended Dosage for Chronic Lymphocytic Leukemia (CLL)

All patients must receive at least one full dose of a rituximab product by intravenous infusion in combination with FC chemotherapy before starting treatment with RITUXAN HYCELA [see Dosage and Administration (2.1) and Warnings and Precautions (5.4)]. Premedicate before each dose [see Dosage and Administration (2.5)].

The recommended dose for CLL is RITUXAN HYCELA 1,600 mg/26,800 Units (1,600 mg rituximab and 26,800 Units hyaluronidase human) in combination with FC chemotherapy, at a fixed dose, irrespective of patient's body surface area. Administer RITUXAN HYCELA 1,600 mg/26,800 Units on Day 1 of Cycles 2–6 (every 28 days) for a total of 5 cycles following a full intravenous dose at Day 1, Cycle 1 (i.e., 6 cycles in total).

2.5 Recommended Premedication and Prophylactic Medications

Premedicate with acetaminophen and an antihistamine before each dose of RITUXAN HYCELA. Premedication with a glucocorticoid should also be considered [see Dosage and Administration (2.2, 2.3, 2.4)].

Provide prophylaxis for Pneumocystis jiroveci pneumonia (PCP) and herpes virus infections for patients with CLL during treatment and for up to 12 months following treatment as appropriate [see Warnings and Precautions (5.6)].

2.6 Preparation and Administration

To prevent medication errors, check the vial labels to ensure that the drug being prepared and administered is RITUXAN HYCELA for subcutaneous use. Do not administer RITUXAN HYCELA intravenously.

RITUXAN HYCELA is ready to use.

Preparation

Use a sterile needle and syringe to prepare RITUXAN HYCELA. RITUXAN HYCELA is compatible with polypropylene and polycarbonate syringe material and stainless steel transfer and injection needles.

Using a 20 mL syringe, withdraw the required volume from the vial with a narrow (e.g., 25–30 gauge) needle of any length.

Label the syringe with the provided peel-off label.

Change the needle to a 1/2" to 5/8" long, narrow gauge needle (e.g., 25–30 gauge) immediately prior to subcutaneous administration to avoid needle clogging.

Visually inspect for particulate matter and discoloration prior to administration. RITUXAN HYCELA should be a clear to opalescent and colorless to yellowish liquid. Do not use if particulates or discoloration is present.

Administration

- Inject RITUXAN HYCELA into the subcutaneous tissue of the abdomen over approximately 5–7 minutes. Never inject into areas where the skin is red, bruised, tender or hard, or areas where there are moles or scars. No data are available on performing the injection at other sites of the body.
- Inject 11.7 mL of RITUXAN HYCELA 1,400 mg/23,400 Units vial (1,400 mg rituximab and 23,400 Units hyaluronidase human) subcutaneously into the abdomen over approximately 5 minutes.
- Inject 13.4 mL of RITUXAN HYCELA 1,600 mg/26,800 Units vial (1,600 mg rituximab and 26,800 Units hyaluronidase human) subcutaneously into the abdomen over approximately 7 minutes.

If administration of RITUXAN HYCELA is interrupted, continue administering at the same site, or at a different site, but restricted to the abdomen.

Observe patients for at least 15 minutes following RITUXAN HYCELA administration [see Warnings and Precautions (5.4)].

During treatment with RITUXAN HYCELA, do not administer other medications for subcutaneous use at the same sites as RITUXAN HYCELA.

Storage

Use immediately.

If not used immediately store refrigerated at 2°C to 8°C (36°F to 46°F) up to 48 hours and subsequently for 8 hours at room temperature up to 30°C (86°F) in diffuse light.

3 DOSAGE FORMS AND STRENGTHS

RITUXAN HYCELA is a colorless to yellowish, clear to opalescent solution for subcutaneous injection:

- Injection: 1,400 mg rituximab and 23,400 Units hyaluronidase human per 11.7 mL (120 mg/2,000 Units per mL) in a single-dose vial.
- Injection: 1,600 mg rituximab and 26,800 Units hyaluronidase human per 13.4 mL (120 mg/2,000 Units per mL) in a single-dose vial.

4 CONTRAINDICATIONS

None

5 WARNINGS AND PRECAUTIONS

5.1 Severe Mucocutaneous Reactions

Mucocutaneous reactions, some with fatal outcome, can occur in patients treated with rituximab-containing products, including RITUXAN HYCELA. These reactions include paraneoplastic pemphigus, Stevens-Johnson syndrome, lichenoid dermatitis, vesiculobullous dermatitis, and toxic epidermal necrolysis. Discontinue RITUXAN HYCELA in patients who experience a severe mucocutaneous reaction. The safety of re-administration of a rituximab-containing product, including RITUXAN HYCELA, to patients with severe mucocutaneous reactions has not been determined.

5.2 Hepatitis B Virus Reactivation

Hepatitis B virus (HBV) reactivation, in some cases resulting in fulminant hepatitis, hepatic failure and death, can occur in patients treated with drugs classified as CD20-directed cytolytic antibodies, including rituximab-containing products. HBV reactivation is defined as an abrupt increase in HBV replication manifesting as a rapid increase in serum HBV DNA levels or detection of HBsAg in a person who was previously HBsAg negative and anti-HBc positive. Reactivation of HBV replication is often followed by hepatitis, i.e., increase in transaminase levels. In severe cases increase in bilirubin levels, liver failure, and death can occur.

Screen all patients for HBV infection by measuring HBsAg and anti-HBc before initiating treatment with a rituximab-containing product. For patients who show evidence of prior hepatitis B infection (HBsAg positive [regardless of antibody status] or HBsAg negative but anti-HBc positive), consult with physicians with expertise in managing hepatitis B regarding monitoring and consideration for HBV antiviral therapy before and/or during treatment with a rituximab-containing product. Monitor patients with evidence of current or prior HBV infection for clinical and laboratory signs of hepatitis or HBV reactivation during and for several months following RITUXAN HYCELA. HBV reactivation has been reported up to 24 months following completion of therapy containing rituximab.

In patients who develop reactivation of HBV while on RITUXAN HYCELA, immediately discontinue treatment and any concomitant chemotherapy, and institute appropriate treatment. Insufficient data exist regarding the safety of resuming RITUXAN HYCELA treatment in patients who develop HBV reactivation. Resumption of RITUXAN HYCELA treatment in patients whose HBV reactivation resolves should be discussed with physicians with expertise in managing HBV.

5.3 Progressive Multifocal Leukoencephalopathy (PML)

JC virus infection resulting in PML and death has been observed in patients receiving rituximab-containing products, including RITUXAN HYCELA. Consider the diagnosis of PML in any patient presenting with new-onset neurologic manifestations. Evaluation of PML includes, but is not limited to, consultation with a neurologist, brain MRI, and lumbar puncture.

Discontinue RITUXAN HYCELA and consider discontinuation or reduction of any concomitant chemotherapy or immunosuppressive therapy in patients who develop PML [see Adverse Reactions (6.1)].

5.4 Hypersensitivity and other Administration Reactions

Systemic Reactions

Patients must receive at least one full dose of a rituximab product by intravenous infusion before receiving RITUXAN HYCELA due to the higher risk of hypersensitivity and other acute reactions during the first infusion [see Dosage and Administration (2.1)]. Beginning therapy with a rituximab product by intravenous infusion allows management of hypersensitivity and other administration reactions by slowing or stopping the intravenous infusion.

Rituximab-containing products, including RITUXAN HYCELA, are associated with hypersensitivity and other administration reactions, which may be related to release of cytokines and/or other chemical mediators. Cytokine release syndrome may be clinically indistinguishable from acute hypersensitivity reactions.

This set of reactions which includes syndrome of cytokine release, tumor lysis syndrome and anaphylactic and hypersensitivity reactions are described below. They are not specifically related to the route of administration of a rituximab-containing product.

Severe infusion-related reactions with fatal outcome have been reported with the use of intravenous formulations of rituximab products, with an onset ranging within 30 minutes to 2 hours after starting the first intravenous infusion. They were characterized by pulmonary events in addition to fever, chills, rigors, hypotension, urticaria, angioedema and other symptoms.

Anaphylactic and other hypersensitivity reactions can also occur. In contrast to cytokine release syndrome, true hypersensitivity reactions typically occur within minutes after starting infusion.

Severe cytokine release syndrome is characterized by severe dyspnea, often associated by bronchospasm and hypoxia, in addition to fever, chills, rigors, urticaria, and angioedema. This syndrome may be associated with acute respiratory failure and death [see Warnings and Precautions (5.5)]. Cytokine release syndrome may occur within 1–2 hours of initiating the infusion. Patients with a history of pulmonary insufficiency or those with pulmonary tumor infiltration may be at a greater risk of poor outcome. Rituximab product administration should be interrupted immediately and aggressive symptomatic treatment initiated.

During RITUXAN HYCELA administration, the injection should be interrupted immediately when observing signs of a severe reaction and aggressive symptomatic treatment should be initiated.

Closely monitor the following patients: those with pre-existing cardiac or pulmonary conditions, those who experienced prior cardiopulmonary adverse reactions, and those with high numbers of circulating malignant cells (≥ 25,000/mm^3) [see Warnings and Precautions (5.5, 5.7)].

Premedicate patients with an antihistamine and acetaminophen prior to each administration of RITUXAN HYCELA [see Dosage and Administration (2.5)]. Premedication with glucocorticoids should also be considered. Observe patients for at least 15 minutes following RITUXAN HYCELA. A longer period may be appropriate in patients with an increased risk of hypersensitivity reactions.

Local Cutaneous Reactions

Local cutaneous reactions, including injection site reactions, have been reported in patients receiving RITUXAN HYCELA. Symptoms included pain, swelling, induration, hemorrhage, erythema, pruritus, and rash [see Adverse Reactions (6.1)]. Some local cutaneous reactions occurred more than 24 hours after RITUXAN HYCELA administration. The incidence of local cutaneous reactions following administration of RITUXAN HYCELA was 16%. Reactions were mild or moderate and resolved without any specific treatment. Local cutaneous reactions of any Grade were most common during the first RITUXAN HYCELA cycle (Cycle 2; 5%) with the incidence decreasing with subsequent injections.

5.5 Tumor Lysis Syndrome (TLS)

TLS can occur within 12–24 hours after administration of a rituximab-containing product, including RITUXAN HYCELA. A high number of circulating malignant cells (≥ 25,000/mm^3) or high tumor burden confers a greater risk of TLS. Administer aggressive intravenous hydration and anti-hyperuricemic therapy in patients at high risk for TLS. Correct electrolyte abnormalities, monitor renal function and fluid balance, and administer supportive care, including dialysis as indicated [see Warnings and Precautions (5.8)].

5.6 Infections

Serious, including fatal, bacterial, fungal, and new or reactivated viral infections can occur during and following the completion of therapy with rituximab-containing products, including RITUXAN HYCELA. The incidence of infections with RITUXAN HYCELA vs rituximab was 56% and 49% respectively in patients with CLL, and 46% and 41% respectively in patients with FL/DLBCL in combination with chemotherapy. Infections have been reported in some patients with prolonged hypogammaglobulinemia (defined as hypogammaglobulinemia > 11 months after rituximab exposure). New or reactivated viral infections included cytomegalovirus, herpes simplex virus, parvovirus B19, varicella zoster virus, West Nile virus, and hepatitis B and C. Discontinue RITUXAN HYCELA for serious infections and institute appropriate anti-infective therapy [see Adverse Reactions (6.1)].

5.7 Cardiovascular Adverse Reactions

Cardiac adverse reactions, including ventricular fibrillation, myocardial infarction, and cardiogenic shock may occur with rituximab-containing products, including RITUXAN HYCELA.

Discontinue RITUXAN HYCELA for serious or life threatening cardiac arrhythmias. Perform cardiac monitoring during and after all administrations of RITUXAN HYCELA for patients who develop clinically significant arrhythmias, or who have a history of arrhythmia or angina [see Adverse Reactions (6.1)].

5.8 Renal Toxicity

Severe, including fatal, renal toxicity can occur after administration of rituximab-containing products, including RITUXAN HYCELA. Renal toxicity has occurred in patients who experience tumor lysis syndrome and in patients with administered concomitant cisplatin therapy during clinical trials. The combination of cisplatin and RITUXAN HYCELA is not an approved treatment regimen. Monitor closely for signs of renal failure and discontinue RITUXAN HYCELA in patients with a rising serum creatinine or oliguria [see Warnings and Precautions (5.5)].

5.9 Bowel Obstruction and Perforation

Abdominal pain, bowel obstruction and perforation, in some cases leading to death, can occur in patients receiving rituximab-containing products, including RITUXAN HYCELA, in combination with chemotherapy. In postmarketing reports, the mean time to documented gastrointestinal perforation was 6 (range 1–77) days. Evaluate if symptoms of obstruction such as abdominal pain or repeated vomiting occur.

5.10 Immunization

The safety of immunization with live viral vaccines following rituximab-containing products, including RITUXAN HYCELA, therapy has not been studied and vaccination with live virus vaccines is not recommended before or during treatment.

5.11 Embryo-Fetal Toxicity

Based on human data, rituximab-containing products can cause fetal harm due to B-cell lymphocytopenia in infants exposed to rituximab in-utero. Advise pregnant women of the potential risk to a fetus. Advise females of reproductive potential to use effective contraception during treatment with RITUXAN HYCELA and for 12 months after the last dose of rituximab-containing products, including RITUXAN HYCELA [see Use in Specific Populations (8.1, 8.3)].

6 ADVERSE REACTIONS

The following clinically significant adverse reactions are described elsewhere in the labeling:

- Mucocutaneous reactions [see Warnings and Precautions (5.1)]
- Hepatitis B reactivation including fulminant hepatitis [see Warnings and Precautions (5.2)]
- Progressive multifocal leukoencephalopathy [see Warnings and Precautions (5.3)]
- Hypersensitivity and other administration reactions [see Warnings and Precautions (5.4)]
- Tumor lysis syndrome [see Warnings and Precautions (5.5)]
- Infections [see Warnings and Precautions (5.6)]
- Cardiac arrhythmias [see Warnings and Precautions (5.7)]
- Renal toxicity [see Warnings and Precautions (5.8)]
- Bowel obstruction and perforation [see Warnings and Precautions (5.9)]

6.1 Clinical Trials Experience

Because clinical trials are conducted under widely varying conditions, adverse reaction rates observed in the clinical trials of a drug cannot be directly compared to rates in the clinical trials of another drug and may not reflect the rates observed in clinical practice.

The data described below reflect exposure to RITUXAN HYCELA in 892 patients in four controlled trials with exposures ranging from a single injection up to 27 months of treatment.

The population included 382 patients with follicular lymphoma (FL), 369 patients with diffuse large B-cell lymphoma (DLBCL), and 141 patients with chronic lymphocytic leukemia (CLL). The median age was 60 years (range: 18–85 years, 53% were male, and 84% were White. In the SABRINA study patients with FL received a full dose of a rituximab product by intravenous infusion, followed by RITUXAN HYCELA (1,400 mg rituximab/23,400 Units hyaluronidase human), in combination with chemotherapy for up to 7 doses (i.e., total of 8 doses in combination with chemotherapy), or as monotherapy for up to 12 doses (maintenance treatment). In the MabEase study patients with DLBCL received a full dose of a rituximab product by intravenous infusion, followed by RITUXAN HYCELA (1,400 mg rituximab/23,400 Units hyaluronidase human), given in combination with chemotherapy for up to 7 doses (i.e., up to a total of 8 doses). In the SAWYER study patients with CLL on part 2 received a full dose of a rituximab product by intravenous infusion, followed by RITUXAN HYCELA (1,600 mg rituximab/26,800 Units hyaluronidase human) for up to 5 doses, in combination with fludarabine and cyclophosphamide (i.e., total of 6 doses).

The most common adverse reactions (≥ 20%) of RITUXAN HYCELA observed in patients with FL on the SABRINA study were: infections, neutropenia, nausea, constipation, cough, and fatigue.

The most common adverse reactions (≥ 20%) of RITUXAN HYCELA observed in patients with DLBCL on the MabEase study were: infections, neutropenia, alopecia, nausea, and anemia.

The most common adverse reactions (≥ 20%) of RITUXAN HYCELA observed in patients with CLL on part 2 of the SAWYER study were: infections, neutropenia, nausea, thrombocytopenia, pyrexia, vomiting, and injection site erythema.

Administration-related reactions (ARRs)

Administration-related reactions (ARRs) with RITUXAN HYCELA were defined as all the adverse reactions related to the administration of RITUXAN HYCELA within the 24 hours post injection.

The incidence of ARRs with RITUXAN HYCELA was 34% in FL/DLBCL in combination with chemotherapy with injection site erythema (5%), chills (3%), dyspnea, erythema, flushing, injection site pain, nausea, pruritus, pyrexia, rash, and throat irritation (2% each) being the most common ARRs. The incidence of ARRs in FL maintenance setting was 20%. The most common ARRs were injection site erythema (7%), erythema (4%), injection site pain/edema, myalgia, and rash (2% each).

The incidence of ARRs with RITUXAN HYCELA in CLL was 44%.

With the exception of Local Cutaneous Reactions, the incidence and profile of adverse reactions reported for RITUXAN HYCELA were comparable with those for rituximab. The overall incidence of adverse reactions for intravenous rituximab versus RITUXAN HYCELA in combination with chemotherapy for FL/DLBCL was 93% versus 95% (BSA ≤ 1.73 m^2), 89% versus 93% (1.73 < BSA ≤ 1.92 m^2), and 94% versus 94% (BSA > 1.92 m^2). The overall incidence of adverse reactions for rituximab versus RITUXAN HYCELA in CLL was 89% versus 100% (BSA ≤ 1.81 m^2), 97% versus 88% (1.82 < BSA ≤ 1.99 m^2), and 88% versus 93% (BSA > 2.00 m^2).

Summary of Clinical Trial Experience in Follicular Lymphoma (FL)

The data in Table 1 were obtained in the SABRINA study, a two-stage randomized, controlled study in patients with previously untreated FL. The study compared patients receiving RITUXAN HYCELA (1,400 mg rituximab/23,400 Units hyaluronidase human; n=197) with patients receiving a rituximab product by intravenous infusion (375 mg/m^2; n=210), both in combination with CHOP or CVP followed by maintenance treatment with RITUXAN HYCELA or a rituximab product by intravenous infusion.

The majority of patients completed all 8 cycles of combination treatment with chemotherapy (91% RITUXAN HYCELA vs. 90% rituximab). In addition, 69% of patients in each of the treatment groups completed all 20 cycles of combination plus maintenance treatment. In both RITUXAN HYCELA and rituximab groups, patients experienced similar median duration of exposure (27.1 months for each arm).

Across the two stages, the overall demographics and baseline characteristics were balanced between the treatment groups. However, there were more female patients (53%) randomized in the study than male patients (47%) and a higher proportion of females were randomized to receive RITUXAN HYCELA (59% female) compared with the rituximab group (48%). The treatment groups in the combined Stage 1 and 2 population were otherwise balanced in regard to baseline demographics, characterized by a median age of 57 years (56.0 years [range 28–85 years] for RITUXAN HYCELA and 57 years [range 28–86 years] for rituximab) and median BSA of 1.83 m^2 (1.80 and 1.84 m^2 for RITUXAN HYCELA and rituximab, respectively).

The incidence of all adverse reactions was 96% for RITUXAN HYCELA vs. 95% for rituximab (Table 1). Grade 3–4 adverse reactions were reported in 55% of patients receiving RITUXAN HYCELA vs. 53% in patients receiving rituximab. Serious adverse reactions were reported in 37% of patients receiving RITUXAN HYCELA vs. 34% of patients receiving rituximab. The most common adverse reactions (occurring in ≥ 20% of patients in any arm) were infections, neutropenia, nausea, constipation, cough, and fatigue.

A total of 36 patients died, including 14/197 patients (7%) who received RITUXAN HYCELA and 22/210 patients (10%) who received rituximab. Of these 36 patients, 19 patients (7 patients RITUXAN HYCELA [4%] vs. 12 patients rituximab [6%]) died due to adverse reactions and 13 patients (6 patients RITUXAN HYCELA [3%] vs. 7 patients rituximab [3%]) died due to disease progression.

The incidence of administration-related reactions (ARRs) due to the subcutaneous route of administration associated with RITUXAN HYCELA was assessed in combination with chemotherapy and during maintenance. Thirty patients (15%) experienced an ARR during the first administration of RITUXAN HYCELA (Cycle 2). Incidence of ARRs generally decreased at subsequent cycles with 18 patients (9%) reporting ARR at Cycle 3, 13 patients (7%) at Cycle 4, 11 patients (6%) at Cycles 5 and 6, 12 patients (7%) at Cycle 7, and 8 patients (4%) at Cycle 8. During RITUXAN HYCELA monotherapy in the maintenance setting the incidence of ARRs at each cycle was ≤ 7% and was observed in 24 patients (14%) overall. Grade 1–2 ARRs constituted 96% of the overall ARRs. Grade 3 ARRs were reported during the first administration of RITUXAN HYCELA at Cycle 2 by 2 patients. Of the reported ARRs, local cutaneous reactions with RITUXAN HYCELA were reported in 32 patients. These events resolved within a median of 2 days from the onset (range 1 to 37 days). Majority of these reactions were Grade 1 and 2 and were observed in 31 patients (16%).

Table 1: Incidence of Adverse Reactions in ≥ 5% of Patients with Previously Untreated Follicular Lymphoma Receiving RITUXAN HYCELA or Rituximab in Combination with CHOP or CVP and as Monotherapy for Maintenance Treatment
Body System/Adverse Reactions | RITUXAN HYCELA (n=197) |  | Rituximab (n=210)
Body System/Adverse Reactions | All Grades % | Grade 3–4 % | All Grades % | Grade 3–4 %
Gastrointestinal Disorders
Nausea | 31 | 0 | 22 | 0
Constipation | 25 | 0 | 26 | < 1
Diarrhea | 18 | 2 | 16 | < 1
Abdominal Pain | 14 | 0 | 12 | < 1
Vomiting | 14 | 0 | 12 | < 1
Dyspepsia | 8 | 0 | 7 | 0
Stomatitis | 6 | 0 | 5 | 0
Abdominal Pain Upper | 5 | 0 | 5 | 0
General Disorders and Administration Site Conditions
Fatigue | 20 | 0 | 18 | < 1
Asthenia | 17 | 1 | 13 | 0
Pyrexia | 15 | < 1 | 16 | < 1
Injection Site Erythema | 13 | 0 | 0 | 0
Injection Site Pain | 8 | 0 | 0 | 0
Chills | 8 | 0 | 9 | 0
Chest Pain | 6 | 1 | 3 | 0
Edema Peripheral | 5 | < 1 | 6 | 0
Mucosal Inflammation | 5 | 1 | 6 | < 1
Influenza Like Illness | 3 | 0 | 6 | 0
Infections
Upper Respiratory Tract Infection | 15 | < 1 | 10 | 0
Pneumonia | 11 | 5 | 4 | 2
Nasopharyngitis | 10 | 0 | 10 | 0
Bronchitis | 8 | < 1 | 8 | < 1
Urinary Tract Infection | 8 | 1 | 14 | < 1
Sinusitis | 7 | < 1 | 4 | 0
Conjunctivitis | 5 | 0 | 5 | 0
Influenza | 4 | 0 | 6 | < 1
Blood and Lymphatic System Disorders
Neutropenia | 32 | 26 | 27 | 21
Anemia | 15 | 5 | 13 | 0
Febrile Neutropenia | 8 | 7 | 6 | 6
Leukopenia | 6 | 4 | 11 | 2
Musculoskeletal and Connective Tissue Disorders
Arthralgia | 13 | < 1 | 10 | 0
Bone Pain | 10 | < 1 | 8 | 0
Pain In Extremity | 10 | 0 | 5 | 0
Back Pain | 9 | < 1 | 12 | < 1
Muscle Spasms | 8 | 0 | 3 | 0
Myalgia | 8 | 0 | 5 | 0
Nervous System Disorders
Paresthesia | 16 | 0 | 12 | 0
Headache | 13 | 0 | 9 | 0
Neuropathy Peripheral | 12 | 2 | 14 | < 1
Dizziness | 7 | 0 | 7 | 0
Skin and Subcutaneous Tissue Disorders
Alopecia | 14 | < 1 | 10 | < 1
Pruritus | 10 | 0 | 12 | < 1
Rash | 10 | 0 | 7 | 0
Erythema | 9 | 0 | 5 | 0
Respiratory, Thoracic and Mediastinal Disorders
Cough | 23 | 0 | 13 | < 1
Dyspnea | 11 | 1 | 8 | 2
Oropharyngeal Pain | 9 | 0 | 8 | 0
Psychiatric Disorders
Insomnia | 9 | 0 | 9 | 0
Vascular Disorders
Hypertension | 6 | 1 | 6 | 0

Summary of Clinical Trial Experience in Diffuse Large B-Cell Lymphoma (DLBCL)

The data in Table 2 were obtained in the MabEASE study, a comparative, randomized, parallel-group, multicenter study to investigate the efficacy of RITUXAN HYCELA (1,400 mg rituximab and 23,400 Units hyaluronidase human; n=369) versus 375 mg/m^2 a rituximab product by intravenous infusion (n=203) both in combination with CHOP (R-CHOP) in previously untreated patients with CD20-positive DLBCL.

Eighty two percent of patients receiving RITUXAN HYCELA or rituximab completed all 8 cycles of study treatment. In both RITUXAN HYCELA and rituximab treatment groups, patients experienced 4.9 months median duration of rituximab exposure in each arm.

The demographic characteristics were balanced. Most patients were White (79%) and 54% were male. The median was 64 years and median BSA was 1.83 m^2.

The incidences of adverse reactions of any grade (RITUXAN HYCELA [94%] vs. rituximab [92%]) (Table 2), Grade 3–4 adverse reactions (RITUXAN HYCELA [63%] vs. rituximab [57%]), and serious adverse reactions (RITUXAN HYCELA [42%] vs. rituximab [37%]) were generally comparable between the two treatment groups. The common adverse reactions (occurring in ≥ 20% of patients in any treatment group) were neutropenia, alopecia, nausea, and anemia.

A total of 91 patients (16%) died, including 58/369 patients (16%) in RITUXAN HYCELA and 33/203 patients (16%) in rituximab. Of these patients, 44 patients (29 patients RITUXAN HYCELA [8%] vs. 15 patients rituximab [7%]) died due to adverse reactions and 35 patients (22 patients RITUXAN HYCELA [6%] vs. 13 patients rituximab [6%]) died due to disease progression. Pneumonia (4 patients RITUXAN HYCELA vs. 1 patient rituximab), septic shock (2 patients RITUXAN HYCELA vs. 3 patients rituximab), and cardiac arrest (1 patient RITUXAN HYCELA vs. 3 patients rituximab) were the most common adverse reactions leading to death.

The incidence of administration-related reactions was balanced between the RITUXAN HYCELA and rituximab groups (28% vs. 29%). Grade 1–2 ARRs constituted 97% of the overall ARRs for the RITUXAN HYCELA arm and 80% for the rituximab arm. Of the reported ARRs, local cutaneous reactions with RITUXAN HYCELA were reported in 17 patients. These events resolved within a median of 2 days from the onset (range 1 to 32 days). Majority of these reactions were Grade 1 and 2 and were observed in 16 patients (4%).

Table 2: Incidence of Adverse Reactions in ≥ 5% of Patients with Previously Untreated DLBCL Receiving RITUXAN HYCELA or Rituximab in Combination with CHOP
Body System/Adverse Reactions | RITUXAN HYCELA + CHOP (n=369) |  | Rituximab + CHOP (n=203)
Body System/Adverse Reactions | All Grades % | Grade 3–4 % | All Grades % | Grade 3–4 %
Gastrointestinal Disorders
Nausea | 22 | < 1 | 24 | < 1
Constipation | 15 | < 1 | 17 | < 1
Diarrhea | 14 | 1 | 10 | 1
Vomiting | 11 | < 1 | 8 | < 1
Abdominal Pain | 7 | < 1 | 7 | < 1
Stomatitis | 6 | < 1 | 5 | 0
Dyspepsia | 5 | 0 | 7 | 0
General Disorders and Administration Site Conditions
Fatigue | 19 | 1 | 15 | 1
Pyrexia | 13 | < 1 | 13 | 0
Asthenia | 11 | < 1 | 12 | < 1
Mucosal Inflammation | 8 | < 1 | 8 | 1
Edema Peripheral | 8 | < 1 | 4 | 0
Infections
Pneumonia | 7 | 3 | 4 | 2
Blood and Lymphatic System Disorders
Neutropenia | 31 | 25 | 29 | 19
Anemia | 23 | 5 | 21 | 4
Febrile Neutropenia | 14 | 14 | 12 | 11
Leukopenia | 7 | 3 | 7 | 3
Lymphopenia | 5 | 1 | 6 | 3
Investigations
Neutrophil Count Decreased | 14 | 11 | 14 | 11
White Blood Cell Count Decreased | 7 | 4 | 7 | 5
Weight Decreased | 8 | < 1 | 4 | < 1
Lymphocyte Count Decreased | 5 | 2 | 3 | 2
Metabolism and Nutrition Disorders
Decreased Appetite | 8 | < 1 | 9 | < 1
Nervous System Disorders
Neuropathy Peripheral | 12 | < 1 | 12 | 0
Paresthesia | 9 | < 1 | 6 | 0
Headache | 6 | 0 | 7 | 0
Skin and Subcutaneous Tissue Disorders
Alopecia | 24 | 0 | 24 | 0
Respiratory, Thoracic and Mediastinal Disorders
Cough | 11 | < 1 | 9 | 0
Dyspnea | 6 | 0 | 4 | < 1
Psychiatric Disorders
Insomnia | 7 | < 1 | 6 | < 1

Summary of Clinical Trial Experience in Chronic Lymphocytic Leukemia

The data in Table 3 were obtained in part 2 of the SAWYER study, a two-part, comparative, randomized, parallel-group, multicenter study of RITUXAN HYCELA versus a rituximab product by intravenous infusion both in combination with fludarabine and cyclophosphamide (FC) chemotherapy in patients with previously untreated CLL.

The safety analysis population in part 2 of the study included 85 patients receiving RITUXAN HYCELA (1,600 mg rituximab/26,800 Units hyaluronidase human) and 89 patients receiving 500 mg/m^2 rituximab. In both RITUXAN HYCELA and rituximab groups, patients had similar median duration of rituximab exposure (4.9 vs. 4.7 months). The majority of patients received all 6 cycles of study treatment (86% RITUXAN HYCELA vs. 81% rituximab).

The patient population was predominantly White (96%) and male (65%), with a median age of 60 years and median BSA of 1.9 m^2 (1.97 and 1.86 m^2 for the RITUXAN HYCELA and intravenous rituximab groups, respectively). Overall, the treatment groups were balanced with respect to demographic characteristics, with the exception of more males in the RITUXAN HYCELA arm (71% RITUXAN HYCELA vs. 60% rituximab). Baseline disease characteristics were similar between the two groups. Over half of the patients (62%) had Binet Stage B disease and the majority had typical CLL characterizations (93%), with median time from first CLL diagnosis to randomization being 18.5 months.

The incidences of adverse reactions were balanced between the two treatment groups (96% RITUXAN HYCELA vs. 91% rituximab), and the common adverse reactions (occurring in ≥ 20% of patients in any arm) were infections, neutropenia, nausea, thrombocytopenia, pyrexia, anemia, vomiting, and injection site erythema. The incidences of Grade 3–4 adverse reactions were also balanced between the two treatment groups (69% RITUXAN HYCELA vs. 71% rituximab). The incidence of serious adverse reactions was 29% for RITUXAN HYCELA and 33% for rituximab. The incidence of administration-related reactions was 44% for RITUXAN HYCELA and 45% for rituximab). Of the reported ARRs, local cutaneous reactions with RITUXAN HYCELA were reported in 15 patients. These events resolved within a median of 6 days from the onset (range 3 to 29 days). Majority of these reactions were Grade 1 and 2 and were observed in 14 patients (16%).

A total of 9 patients (5%) died, including 5 patients in the RITUXAN HYCELA group and 4 patients in the rituximab group. In the RITUXAN HYCELA group, 1 patient died due to herpes zoster infection, 1 patient died as a result of progressive multifocal leukoencephalopathy (PML) (considered by the investigator as related to rituximab), and 3 patients died due to disease progression. In the rituximab group, 2 patients died due to diarrhea and listeriosis and 2 patients died due to disease progression.

Table 3: Incidence of Adverse Reactions in ≥ 5% of Patients with Previously Untreated CLL Receiving RITUXAN HYCELA or Rituximab in Combination with FC
Body System/Adverse Reactions | RITUXAN HYCELA + FC (n=85) |  | Rituximab + FC (n=89)
Body System/Adverse Reactions | All Grades % | Grade 3–4 % | All Grades % | Grade 3–4 %
Gastrointestinal Disorders
Nausea | 38 | 1 | 35 | 0
Vomiting | 21 | 2 | 22 | 1
Diarrhea | 12 | 0 | 11 | 3
Abdominal Pain | 9 | 0 | 6 | 0
Constipation | 8 | 0 | 8 | 0
General Disorders and Administration Site Conditions
Pyrexia | 32 | 5 | 25 | 1
Injection Site Erythema | 26 | 2 | 0 | 0
Injection Site Pain | 16 | 1 | 0 | 0
Chills | 13 | 0 | 10 | 1
Fatigue | 11 | 0 | 10 | 0
Asthenia | 8 | 1 | 17 | 2
Infections
Upper Respiratory Tract Infection | 13 | 0 | 12 | 1
Respiratory Tract Infection | 8 | 1 | 4 | 1
Bronchitis | 7 | 0 | 6 | 0
Urinary Tract Infection | 2 | 0 | 8 | 1
Pneumonia | 2 | 2 | 6 | 2
Blood and Lymphatic System Disorders
Neutropenia | 65 | 56 | 58 | 52
Thrombocytopenia | 24 | 6 | 26 | 9
Leukopenia | 19 | 14 | 16 | 12
Anemia | 13 | 5 | 24 | 9
Febrile Neutropenia | 11 | 8 | 8 | 8
Musculoskeletal and Connective Tissue Disorders
Arthralgia | 9 | 0 | 1 | 0
Pain In Extremity | 7 | 1 | 2 | 0
Bone Pain | 6 | 0 | 2 | 0
Nervous System Disorders
Headache | 7 | 0 | 9 | 0
Skin and Subcutaneous Tissue Disorders
Erythema | 15 | 0 | 7 | 0
Rash | 12 | 0 | 10 | 1
Pruritus | 8 | 0 | 4 | 0
Respiratory, Thoracic and Mediastinal Disorders
Cough | 13 | 0 | 11 | 0
Oropharyngeal Pain | 6 | 0 | 3 | 0
Dyspnea | 4 | 0 | 8 | 1
Psychiatric Disorders
Insomnia | 1 | 0 | 7 | 0
Vascular Disorders
Hypotension | 1 | 0 | 7 | 1
Hypertension | 0 | 0 | 6 | 1

6.2 Immunogenicity

As with all therapeutic proteins, there is potential for immunogenicity. The detection of antibody formation is highly dependent on the sensitivity and specificity of the assay. Additionally, the observed incidence of antibody (including neutralizing antibody) positivity in an assay may be influenced by several factors including assay methodology, sample handling, timing of sample collection, concomitant medications, and underlying disease. For these reasons, comparison of the incidence of antibodies to RITUXAN HYCELA and rituximab in the studies described below with the incidence of antibodies in other studies or to other products may be misleading.

In the SABRINA study, where previously untreated patients with follicular lymphoma were treated with RITUXAN HYCELA or rituximab in combination with CVP or CHOP, the incidence of treatment-induced/enhanced anti-rituximab antibodies in the RITUXAN HYCELA group was similar to that observed in the rituximab group (2.0% RITUXAN HYCELA vs. 1.9% rituximab). The incidence of treatment-induced/enhanced anti-recombinant human hyaluronidase antibodies was 15% in the RITUXAN HYCELA group compared with 8% in the rituximab group, and the overall proportion of patients found to have anti-recombinant human hyaluronidase antibodies remained generally constant over the follow-up period in both cohorts. All patients who tested positive for anti-recombinant human hyaluronidase antibodies at any point during the study were negative for neutralizing antibodies.

In the SAWYER study, where previously untreated patients with CLL were treated with RITUXAN HYCELA or rituximab in combination with FC, the incidence of treatment-induced/enhanced anti-rituximab antibodies was 12% in the RITUXAN HYCELA group and 15% in the rituximab group. The incidence of treatment-induced/enhanced anti-recombinant human hyaluronidase antibodies was 11% in the RITUXAN HYCELA treatment arm. None of the patients who tested positive for anti-recombinant human hyaluronidase antibodies tested positive for neutralizing antibodies.

The clinical relevance of the development of anti-rituximab or anti-recombinant human hyaluronidase antibodies after treatment with RITUXAN HYCELA is not known.

6.3 Postmarketing Experience

The following adverse reactions have been identified during post-approval use of rituximab-containing products. Because these reactions are reported voluntarily from a population of uncertain size, it is not always possible to reliably estimate their frequency or establish a causal relationship to drug exposure.

- Hematologic: prolonged pancytopenia, marrow hypoplasia, Grade 3–4 prolonged or late-onset neutropenia, hyperviscosity syndrome in Waldenstrom's macroglobulinemia, prolonged hypogammaglobulinemia
- Cardiac: fatal cardiac failure
- Immune/Autoimmune Events: uveitis, optic neuritis, systemic vasculitis, pleuritis, lupus-like syndrome, serum sickness, polyarticular arthritis, and vasculitis with rash.
- Infection: viral infections, including progressive multifocal leukoencephalopathy (PML), increase in fatal infections in HIV-associated lymphoma, and a reported increased incidence of Grade 3 and 4 infections
- Neoplasia: disease progression of Kaposi's sarcoma.
- Skin: severe mucocutaneous reactions, pyoderma gangrenosum (including genital presentation).
- Gastrointestinal: bowel obstruction and perforation.
- Pulmonary: fatal bronchiolitis obliterans and fatal interstitial lung disease.

8 USE IN SPECIFIC POPULATIONS

8.1 Pregnancy

Risk Summary

Based on human data, rituximab-containing products can cause fetal harm due to B-cell lymphocytopenia in infants exposed to rituximab in-utero (see Clinical Considerations). There are no available data on RITUXAN HYCELA use in pregnant women to inform a drug-associated risk of major birth defects and miscarriage. In animal reproduction studies, intravenous administration of a rituximab product to pregnant cynomolgus monkeys during the period of organogenesis caused lymphoid B cell depletion in the newborn offspring at doses resulting in 80% of the exposure (based on AUC) of those achieved following a dose of 2 grams in humans. Reduced fetal weight and increased fetal lethality were observed following subcutaneous administration of hyaluronidase human in mice at a dose > 2700 times higher than the human dose. Comparable systemic exposure levels could occur in a pregnant patient following accidental intravenous administration of an entire vial of RITUXAN HYCELA (see Data). Advise pregnant women of the potential risk to a fetus.

The estimated background risk of major birth defects and miscarriage for the indicated populations is unknown. All pregnancies have a background risk of birth defect, loss, or other adverse outcomes. The estimated background risk in the U.S. general population of major birth defects is 2%–4% and of miscarriage is 15%–20% of clinically recognized pregnancies.

Clinical Considerations

Fetal/Neonatal Adverse Reactions

Observe newborns and infants for signs of infection and manage accordingly.

Data

Human Data

Postmarketing data indicate that B-cell lymphocytopenia generally lasting less than 6 months can occur in infants exposed to rituximab in-utero. Rituximab was detected postnatally in the serum of infants exposed in-utero.

Animal Data

RITUXAN HYCELA for subcutaneous injection contains rituximab and hyaluronidase human [see Description (11)].

Rituximab Product:

- An embryo-fetal developmental toxicity study was performed on pregnant cynomolgus monkeys. Pregnant animals received rituximab via the intravenous route during early gestation (organogenesis period; post coitum days 20 through 50). Rituximab was administered as loading doses on post coitum (PC) Days 20, 21 and 22, at 15, 37.5 or 75 mg/kg/day, and then weekly on PC Days 29, 36, 43 and 50, at 20, 50 or 100 mg/kg/week. The 100 mg/kg/week dose resulted in 80% of the exposure (based on AUC) of those achieved following a dose of 2 grams in humans. Rituximab crosses the monkey placenta. Exposed offspring did not exhibit any teratogenic effects but did have decreased lymphoid tissue B cells.
- A subsequent pre-and postnatal reproductive toxicity study in cynomolgus monkeys was completed to assess developmental effects including the recovery of B cells and immune function in infants exposed to rituximab in utero. Animals were treated with a loading dose of 0, 15, or 75 mg/kg every day for 3 days, followed by weekly dosing with 0, 20, or 100 mg/kg dose. Subsets of pregnant females were treated from PC Day 20 through postpartum Day 78, PC Day 76 through PC Day 134, and from PC Day 132 through delivery and postpartum Day 28. Regardless of the timing of treatment, decreased B cells and immunosuppression were noted in the offspring of rituximab-treated pregnant animals. The B-cell counts returned to normal levels, and immunologic function was restored within 6 months postpartum.

Hyaluronidase Human:

- In an embryo-fetal study, mice have been dosed daily by subcutaneous injection during the period of organogenesis with hyaluronidase human at dose levels up to 2,200,000 U/kg, which is > 2700 times higher than the human dose. The study found no evidence of teratogenicity. Reduced fetal weight and increased numbers of fetal resorptions were observed, with no effects found at a daily dose of 360,000 U/kg, which is > 450 times higher than the human dose.
- In a peri-and post-natal reproduction study, mice have been dosed daily by subcutaneous injection, with hyaluronidase human from implantation through lactation and weaning at dose levels up to 1,100,000 U/kg, which is > 1,300 times higher than the human dose. The study found no adverse effects on sexual maturation, learning and memory or fertility of the offspring.

8.2 Lactation

There are no data on the presence of hyaluronidase human in human milk or the effect of rituximab on milk production, and there is limited data on the effect of rituximab on the breastfed child. However, rituximab is detected in the milk of lactating cynomolgus monkeys and maternal IgG is present in human breast milk. Rituximab has also been reported to be excreted at low concentrations in human breast milk. Given that the clinical significance of this finding for children is not known, advise women not to breastfeed during treatment with RITUXAN HYCELA and for 6 months after the last dose due to the potential for serious adverse reactions in breastfed children.

8.3 Females and Males of Reproductive Potential

Rituximab-containing products can cause fetal harm [see Use in Specific Populations (8.1)].

Pregnancy Testing

Verify pregnancy status in females of reproductive potential prior to initiating RITUXAN HYCELA.

Contraception

Females

Advise females of reproductive potential to use effective contraception during treatment with RITUXAN HYCELA and for 12 months after the last dose of rituximab-containing products, including RITUXAN HYCELA.

8.4 Pediatric Use

The safety and effectiveness of RITUXAN HYCELA in pediatric patients have not been established.

8.5 Geriatric Use

Of the total number of subjects in the SABRINA, MabEase, and SAWYER studies, 37% were 65 and over, while 10% were 75 and over. No overall differences in safety or effectiveness were observed between these subjects and younger subjects, and other reported clinical experience has not identified differences in responses between the elderly and younger patients, but greater sensitivity of some older individuals cannot be ruled out.

11 DESCRIPTION

RITUXAN HYCELA is a combination of rituximab and hyaluronidase human. Rituximab is a genetically engineered chimeric murine/human monoclonal IgG1 kappa antibody directed against the CD20 antigen. Rituximab has an approximate molecular weight of 145 kD. Rituximab has a binding affinity for the CD20 antigen of approximately 8.0 nM. Rituximab is produced by mammalian cell (Chinese Hamster Ovary) suspension.

Recombinant human hyaluronidase is an endoglycosidase used to increase the dispersion and absorption of co-administered drugs when administered subcutaneously. It is produced by mammalian (Chinese Hamster Ovary) cells containing a DNA plasmid encoding for a soluble fragment of human hyaluronidase (PH20). It is a glycosylated single-chain protein with an approximate molecular weight of 61 kD.

RITUXAN HYCELA (rituximab and hyaluronidase human) injection is a colorless to yellowish, clear to opalescent solution supplied in sterile, preservative-free, single-dose vials for subcutaneous use.

RITUXAN HYCELA is supplied as 1,400 mg rituximab and 23,400 Units hyaluronidase human per 11.7 mL in single-dose vials or 1,600 mg rituximab and 26,800 Units hyaluronidase human per 13.4 mL in single-dose vials. Each mL of solution contains rituximab (120 mg), hyaluronidase human (2,000 Units), L-histidine (0.53 mg), L-histidine hydrochloride monohydrate (3.47 mg), L-methionine (1.49 mg), polysorbate 80 (0.6 mg), α,α-trehalose dihydrate (79.45 mg), and Water for Injection.

12 CLINICAL PHARMACOLOGY

12.1 Mechanism of Action

Rituximab is a monoclonal antibody that targets the CD20 antigen expressed on the surface of pre-B and mature B-lymphocytes. Upon binding to CD20, rituximab mediates B-cell lysis. Possible mechanisms of cell lysis include complement dependent cytotoxicity (CDC) and antibody dependent cell mediated cytotoxicity (ADCC). Hyaluronan is a polysaccharide found in the extracellular matrix of the subcutaneous tissue. It is depolymerized by the naturally occurring enzyme hyaluronidase. Unlike the stable structural components of the interstitial matrix, hyaluronan has a half-life of approximately 0.5 days. Hyaluronidase human increases permeability of the subcutaneous tissue by temporarily depolymerizing hyaluronan. In the doses administered, hyaluronidase human in RITUXAN HYCELA acts locally.

The effects of hyaluronidase human are reversible and permeability of the subcutaneous tissue is restored within 24 to 48 hours.

Hyaluronidase human has been shown to increase the absorption rate of a rituximab product into the systemic circulation when given in the subcutis of Göttingen Minipigs.

12.2 Pharmacodynamics

Peripheral B-cell counts declined to levels below normal following a dose of rituximab by intravenous infusion. In patients treated with rituximab for hematological malignancies, B cell recovery began within 6 months of treatment and generally returned to normal levels within 12 months after completion of therapy, although in some patients this may take longer.

Follicular Lymphoma (FL)

Peripheral B-cell counts decline to levels below normal following the first cycle of rituximab and are maintained during treatment with RITUXAN HYCELA. After stopping RITUXAN HYCELA treatment, B-cell repletion followed similar kinetics to that of rituximab with B-cell repletion beginning after 6 months of stopping treatment, although in some patients this may take longer.

Chronic Lymphocytic Leukemia (CLL)

Following the first cycle of treatment of rituximab, B-cells begin to deplete, with 28% of patients B-cell depleted at pre-dose Cycle 2 in the SAWYER study. An increase in the proportion of B-cell depleted patients was observed with subsequent cycles of RITUXAN HYCELA and by Cycle 6, 96% of patients were depleted. Patients remained B-cell depleted until the month 9 follow-up visit, where signs of repletion were seen.

12.3 Pharmacokinetics

The geometric mean rituximab exposures are provided in Table 4. The pharmacokinetic properties of rituximab following the administration of RITUXAN HYCELA in the approved indications are provided in Table 5. The elimination of rituximab was characterized by a time-dependent process that occurred early in therapy and a time-independent process.

Table 4: Rituximab Exposure Values following Subcutaneous Administration of RITUXAN HYCELA [Pharmacokinetic parameters are presented as geometric mean unless otherwise specified.]
 |  | Study [For study design information, see Clinical Studies (14).] | Cycle | Rituximab
FL [RITUXAN HYCELA 1,400 mg/23,400 Units (1,400 mg rituximab and 23,400 Units hyaluronidase human)] | Cmax, mcg/mL (CV%) | SABRINA | 7 | 237 (29.4)
FL [RITUXAN HYCELA 1,400 mg/23,400 Units (1,400 mg rituximab and 23,400 Units hyaluronidase human)] | Cmax, mcg/mL (CV%) | SABRINA | 18 | 156 (24.7) [Based on predicted values]
FL [RITUXAN HYCELA 1,400 mg/23,400 Units (1,400 mg rituximab and 23,400 Units hyaluronidase human)] | Ctrough, mcg/mL (CV%) | SABRINA | 7 | 122.2 (55.3)
FL [RITUXAN HYCELA 1,400 mg/23,400 Units (1,400 mg rituximab and 23,400 Units hyaluronidase human)] | Ctrough, mcg/mL (CV%) | SABRINA | 18 | 45.5 (53.6)
FL [RITUXAN HYCELA 1,400 mg/23,400 Units (1,400 mg rituximab and 23,400 Units hyaluronidase human)] | AUCTAU, mcg∙day/mL (CV%) | SABRINA | 7 | 3779 (33.7)
FL [RITUXAN HYCELA 1,400 mg/23,400 Units (1,400 mg rituximab and 23,400 Units hyaluronidase human)] | AUCTAU, mcg∙day/mL (CV%) | SABRINA | 18 | 5000 (34.3)
CLL [RITUXAN HYCELA 1,600 mg/26,800 Units (1,600 mg rituximab and 26,800 Units hyaluronidase human)] | Cmax, mcg/mL (CV%) | SAWYER | 6 | 202 (36.1)
CLL [RITUXAN HYCELA 1,600 mg/26,800 Units (1,600 mg rituximab and 26,800 Units hyaluronidase human)] | Ctrough, mcg/mL (CV%) | SAWYER | 5 | 97.5 (42.6)
CLL [RITUXAN HYCELA 1,600 mg/26,800 Units (1,600 mg rituximab and 26,800 Units hyaluronidase human)] | AUCTAU, mcg∙day/mL (CV%) | SAWYER | 5 | 4088 (34.2)

In the SABRINA study, the geometric mean Ctrough in the RITUXAN HYCELA arm was higher than in the rituximab arm with a geometric mean ratio (Ctrough, RITUXAN HYCELA/Ctrough, rituximab) of 1.52 (90% CI: 1.36, 1.70) at Cycle 7 [see Clinical Studies (14.1)].

In the SAWYER study, the geometric mean Ctrough in the RITUXAN HYCELA arm was higher than in the rituximab arm with an adjusted geometric mean ratio of 1.53 (90% CI: 1.27–1.85) at Cycle 5 [see Clinical Studies (14.3)].

Table 5: Pharmacokinetic Parameters of Rituximab following Subcutaneous Administration of RITUXAN HYCELA [Parameters represented as geometric mean (%CV) unless otherwise specified]
 | FL | CLL
Absorption
Absolute Bioavailability [Compared to a rituximab product administered intravenously] | 0.646 (0.634–0.659 [95% CI]) | 0.634 (0.602–0.665)
Distribution
Volume of Central compartment (L) | 4.06 (26) | 4.80 (18)
Apparent Volume of Distribution at steady state [Volume of central compartment and peripheral compartment] (L) | 8.09 (19) | 8.52 (13)
Elimination
Terminal Half-life (days) | 34.1 (27) | 32 (24)
Clearance (L/day) | 0.18 (34) | 0.204 (31)

Specific Populations

The pharmacokinetics of rituximab and hyaluronidase human in children and adolescents is unknown. The effect of either renal or hepatic impairment on the pharmacokinetics of rituximab and hyaluronidase human is unknown.

Drug Interaction Studies

The drug interaction potential of rituximab and hyaluronidase human is unknown.

13 NONCLINICAL TOXICOLOGY

13.1 Carcinogenesis, Mutagenesis, Impairment of Fertility

No long term animal studies have been performed to establish the carcinogenic or mutagenic potential of RITUXAN HYCELA or rituximab, or to determine potential effects on fertility in males or females.

RITUXAN HYCELA contains hyaluronidase human. Hyaluronidases are found in most tissues of the body. Long-term animal studies have not been performed to assess the carcinogenic or mutagenic potential of hyaluronidase human. In addition, when hyaluronidase human was administered to cynomolgus monkeys for 39 weeks at dose levels up to 220,000 U/kg, which is > 90 times higher than the human dose, no evidence of toxicity to the male or female reproductive system was found through periodic monitoring of in-life parameters, e.g., semen analyses, hormone levels, menstrual cycles, and also from gross pathology, histopathology and organ weight data.

14 CLINICAL STUDIES

14.1 Follicular Lymphoma

The SABRINA study [NCT01200758] was a randomized, two-stage, open-label, multicenter study that enrolled a total of 410 patients with previously untreated, CD20-positive follicular lymphoma of Grade 1, 2 or 3a requiring therapy. The study design is identical in stage 1 and 2. Patients were randomized (1:1) to receive either a rituximab product by intravenous infusion 375 mg/m^2 for 8 cycles or 1 cycle of a rituximab product by intravenous infusion 375 mg/m^2 followed by 7 cycles of RITUXAN HYCELA 1,400 mg/23,400 Units (1,400 mg rituximab and 23,400 Units hyaluronidase human) both every 3 weeks in combination with a total of 6–8 cycles of CHOP or 8 cycles of CVP chemotherapy. Patients underwent interim staging after 4 cycles. Patients who received R-CHOP and achieved a CR, CRu, PR or SD at the interim assessment could receive either 4 more cycles of R-CHOP or 2 cycles of R-CHOP followed by 2 cycles of monotherapy with rituximab product or RITUXAN HYCELA depending on randomization arm (i.e., a total of 8 cycles of rituximab product or RITUXAN HYCELA). Patients with at least a PR after combination treatment with chemotherapy continued with single agent maintenance treatment administered every 8 weeks for 24 months with rituximab product or RITUXAN HYCELA as per their randomization (i.e., total of 12 cycles of maintenance treatment).

Randomization was stratified by: underlying chemotherapy backbone (CHOP vs CVP), Follicular Lymphoma International Prognostic Index (FLIPI) (low-risk vs. intermediate-risk vs. high-risk), and region (Europe and North America vs. South and Central America vs Asia).

The main outcome measure for Stage 1 was the estimated ratio of observed rituximab serum Ctrough SC/Ctrough IV at Cycle 7 of combination treatment with chemotherapy every 3 weeks. The main outcome measure for Stage 2 was the investigator-assessed ORR consisting of CR, CRu, and PR at the completion of combination treatment with chemotherapy. Additional outcome measures were CRR (CR and CRu) at the end of completion of combination treatment with chemotherapy, ORR and CRR at the end of completion of maintenance treatment, and time-to-event endpoints (progression-free survival (PFS), and overall survival (OS)).

Of all randomized patients, the median age was 57 years (range: 28 to 86), 53% were female, and 86% were White. The median BSA was 1.83 m^2. 45% had high risk or 34% had intermediate risk FLIPI score, and 54% had Ann Arbor Stage IV disease. Ninety percent of patients completed all 8 cycles of combination treatment with chemotherapy, and 70% of patients completed 20 cycles of both combination and maintenance treatment. Median treatment duration was 27.1 months in both groups. The median number of cycles received was 20 in both groups.

The pharmacokinetic results for the primary endpoint in Stage 1, rituximab Ctrough at Cycle 7 (i.e., 21 days after Cycle 7 rituximab administration), demonstrated that RITUXAN HYCELA 1,400 mg/23,400 Units was non-inferior compared with rituximab at 375 mg/m^2 in patients receiving combination treatment with chemotherapy [see Clinical Pharmacology (12.3)]. The efficacy results are presented in Table 6.

Table 6: Efficacy in Patients with Previously Untreated Follicular Lymphoma (SABRINA Study)
 | RITUXAN HYCELA N=205 | Rituximab N=205
Overall Response Rate at End of combination treatment with chemotherapy [Stage 2 main outcome measure was ORR at the end of combination treatment with chemotherapy; however pooled results which were preplanned are presented in this Table. Response rates based on investigator assessment. Response rates at end of maintenance based on patients who received at least one cycle of maintenance treatment (n).] , [Investigator-assessed ORR (comprising CR, CRu and PR).]
Number of responders (CR/CRu, PR) | 173 | 174
Overall response (CR/CRu, PR) rate (%, [95% CI]) | 84% [79;89] | 85% [79;90]
Difference in overall response rates [Difference in response rates (RITUXAN HYCELA minus rituximab).] [95% CI] | -0.5% [-7.7;6.8]
Number of complete responders (CR/CRu) | 66 | 65
Complete response (CR/CRu) rate (%, [95% CI]) | 32% [26;39] | 32% [25;39]
Difference in complete response rates [95% CI] | 0.0% [-9.3;9.3]
Overall Response Rate at End of Maintenance
Number of patients treated in maintenance (n) | 172 | 178
Number of responders (CR/CRu, PR) | 134 | 139
Overall response (CR/CRu, PR) rate (%, [95% CI]) | 78% [71;84] | 78% [71;84]
Difference in overall response rates [95% CI] | -0.2 [-9.2;8.8]
Number of complete responders (CR/CRu) | 87 | 103
Complete response (CR/CRu) rate (%, [95% CI]) | 51% [43;58] | 58% [50;65]
Difference in complete response rates [95% CI] | -7.3 [-18.0;3.5]
Progression-free survival [At time of final analysis (median follow-up 4.8 years).]
Number of patients with event | 65 (32%) | 71 (35%)
Hazard Ratio [95% CI] (unstratified Cox model) | 0.90 [0.64;1.26]
Overall survival
Number of patients with event | 18 (8.8%) | 26 (12.7%)
Hazard Ratio [95% CI] (unstratified Cox model) | 0.70 [0.38;1.27]

14.2 Diffuse Large B-Cell Lymphoma (DLBCL)

The MabEase study [NCT01649856] enrolled a total of 576 patients with previously untreated CD20-positive DLBCL. Patients were randomized (2:1) to receive either a rituximab product by intravenous infusion, 375 mg/m^2 for 8 cycles or 1 cycle of a rituximab product by intravenous infusion 375 mg/m^2 followed by 7 cycles of RITUXAN HYCELA 1,400 mg/23,400 Units (1,400 mg rituximab and 23,400 Units hyaluronidase human), both in combination with up to 6–8 cycles of CHOP chemotherapy, every 14 (CHOP-14) or 21 days (CHOP-21). Randomization was stratified by: age (< 60 years, ≥ 60 years), International Prognostic Index (IPI) risk category (low, low-intermediate, high-intermediate, high), and chemotherapy regimen (CHOP-21 or CHOP-14). The main outcome measure was investigator-assessed complete response rate (CR/CRu) at the end of combination treatment with chemotherapy. Additional outcome measures were time-to-event endpoints (PFS and OS).

Of all randomized patients, the median age was 64 years (range: 18 to 80 years); 54% were male; and 79% were White. The median BSA was 1.83 m^2. 31% low risk or 30% low intermediate risk IPI score, 24% high intermediate risk, or 15% high risk IPI score and 42% of patients had Ann Arbor Stage IV disease. A total of 470 patients (82%) received 8 cycles of treatment. Median duration of exposure to treatment was 4.9 months in both treatment groups. The median number of administrations/cycles (RITUXAN HYCELA or rituximab) was 8 in both groups.

The efficacy results for are presented in Table 7. The median observation time was approximately 28 months.

Table 7: Efficacy in Patients with Previously Untreated DLBCL (MabEase Study)
 | RITUXAN HYCELA N=381 | Rituximab N=195
Complete Response Rate (CR/CRu) [Investigator-assessed.]
Number achieving CR/CRu [Four patients in the RITUXAN HYCELA group and 1 patient in the rituximab group had their response downgraded due to their bone marrow data.] | 179 | 82
Cr/CRu rate (%, [95% CI]) | 47% [42;52] | 42% [35;49]
Difference in rates [95% CI] [Difference in response rates (RITUXAN HYCELA minus rituximab).] | 4.9% [-3.6;13.5]
Progression-free survival [Progression-free survival is defined as the time from randomization to the first occurrence of disease progression or relapse, or death from any cause.]
Number of patients with event | 104 (27%) | 44 (23%)
Hazard Ratio [95% CI] (unstratified Cox model) | 1.22 [0.85;1.73]
Overall survival [Overall survival is defined as the time from randomization until death from any cause.]
Number of patients with event | 63 (17%) | 29 (15%)
Hazard Ratio [95% CI] (unstratified Cox model) | 1.08 [0.70;1.68]

14.3 Chronic Lymphocytic Leukemia (CLL)

The SAWYER study [NCT01292603] was a randomized, two-part, open-label, multicenter study that enrolled a total of 176 patients with previously untreated CLL. Patients were randomized (1:1) to receive either a rituximab product by intravenous infusion, 375 mg/m^2, in Cycle 1 followed by up to 5 cycles of rituximab, 500 mg/m^2, or rituximab, 375 mg/m^2, in Cycle 1 followed by subsequent cycles (2–6) of RITUXAN HYCELA 1,600 mg/26,800 Units (1,600 mg rituximab and 26,800 Units hyaluronidase human), both in combination with fludarabine and cyclophosphamide (FC) chemotherapy. The main outcome measure was the non-inferiority of the pharmacokinetic profile of RITUXAN HYCELA compared to rituximab. An additional outcome measure in Part 2 was investigator-assessed response rate.

The median age was 60 years (range: 25 to 78); 65% were males and 96% were White. The median BSA was 1.9 m^2, 62% had Binet Stage B disease and 93% had typical CLL characterization.

The pharmacokinetic results demonstrated that RITUXAN HYCELA 1,600 mg/26,800 Units serum rituximab Ctrough level was non-inferior compared with rituximab at 500 mg/m^2 in patients receiving combination treatment with chemotherapy [see Clinical Pharmacology (12.3)].

The efficacy results for Part 2 are presented in Table 8.

Table 8: Efficacy in Patients with Previously Untreated CLL (SAWYER Study)
 |  | Part 2
 |  | RITUXAN HYCELA (N = 88) | Rituximab (N = 88)
ORR [At 3 month follow-up visit (Part 2). Investigator-assessed.] | Point estimate | 85.2% (n = 75) | 80.7% (n = 71)
ORR [At 3 month follow-up visit (Part 2). Investigator-assessed.] | 95% CI | [76.1%, 91.9%] | [70.9%, 88.3%]
CRR | Point estimate | 27.3% (n = 24) | 31.8% (n = 28)
CRR | 95% CI | [18.3%, 37.8%] | [22.3%, 42.6%]
PFS [At time of final analysis (median follow-up 4.4 years). Investigator-assessed.] | Proportion with PFS event | 34.1% (n = 30) | 42.0% (n = 37)
PFS [At time of final analysis (median follow-up 4.4 years). Investigator-assessed.] | HR 95% CI | 0.76 [0.47%, 1.23%]
ORR – Overall Response Rate
CRR – Complete Response Rate
PFS – Progression-Free Survival

14.4 Patient Experience

Previously untreated adult patients outside of the United States with CD20+ diffuse large B-cell lymphoma (DLBCL) or CD20+ follicular non-Hodgkin's lymphoma (FL) Grades 1, 2, or 3a were randomized to receive a standard chemotherapy regimen (CHOP, CVP, or bendamustine) and either RITUXAN HYCELA 1,400 mg/23,400 Units at Cycles 2–4 (after the first cycle with intravenous rituximab) or a rituximab product by intravenous infusion at Cycles 1–4. After the fourth cycle, patients were crossed over to the alternative route of administration for the remaining 4 cycles. After Cycle 8, 477 of 620 patients (77%) reported preferring subcutaneous administration of RITUXAN HYCELA over intravenous rituximab and the most common reason was that administration required less time in the clinic. After Cycle 8, 66 of 620 patients (11%) preferred rituximab intravenous administration and the most common reason was that it felt more comfortable during administration. Forty eight of 620 patients (7.7%) had no preference for the route of administration. Twenty nine subjects of 620 (4.7%) received Cycle 8 but did not complete the preference questionnaire.

16 HOW SUPPLIED/STORAGE AND HANDLING

RITUXAN HYCELA (rituximab and hyaluronidase human) injection, for subcutaneous use is supplied as a sterile preservative-free liquid solution in a single-dose vial. The following configurations are available:

Individually packaged single-dose vials:

- RITUXAN HYCELA 1,400 mg/23,400 Units (NDC 50242-108-01) providing 1,400 mg rituximab and 23,400 Units hyaluronidase human per 11.7 mL
- RITUXAN HYCELA 1,600 mg/26,800 Units (NDC 50242-109-01) providing 1,600 mg rituximab and 26,800 Units hyaluronidase human per 13.4 mL

Storage

Store RITUXAN HYCELA vials in the refrigerator at 2°C to 8°C (36°F to 46°F) in the original carton to protect from light. Do not freeze.

17 PATIENT COUNSELING INFORMATION

Advise the patient to read the FDA-approved patient labeling (Medication Guide).

Severe Mucocutaneous Reactions

Advise patients to contact their healthcare provider immediately for symptoms of severe mucocutaneous reactions, including painful sores or ulcers on the lips or mouth, blisters, peeling skin, rash, and pustules [see Warnings and Precautions (5.1)].

Hepatitis B Virus Reactivation

Advise patients to contact their healthcare provider immediately for symptoms of hepatitis including worsening fatigue or yellow discoloration of skin or eyes [see Warnings and Precautions (5.2)].

Progressive Multifocal Leukoencephalopathy (PML)

Advise patients to contact their healthcare provider immediately for signs and symptoms of PML, including new or changes in neurological symptoms such as confusion, dizziness or loss of balance, difficulty talking or walking, decreased strength or weakness on one side of the body, or vision problems [see Warnings and Precautions (5.3)].

Hypersensitivity and Other Administration Reactions

Inform patients about the signs and symptoms of hypersensitivity and administration-related reactions. Advise patients to contact their healthcare provider immediately to report symptoms of administration-related reactions including dizziness, nausea, chills, fever, vomiting, diarrhea, urticaria, angioedema, breathing problems, or chest pain [see Warnings and Precautions (5.4)].

Tumor Lysis Syndrome (TLS)

Advise patients to contact their healthcare provider immediately for signs and symptoms of tumor lysis syndrome such as nausea, vomiting, diarrhea, and lethargy [see Warnings and Precautions (5.5)].

Infections

Advise patients to contact their healthcare provider immediately for signs and symptoms of infections including fever, cold symptoms (e.g., rhinorrhea or laryngitis), flu symptoms (e.g., cough, fatigue, body aches), earache or headache, dysuria, cold sores, and painful wounds with erythema [see Warnings and Precautions (5.6)]

Cardiovascular Adverse Reactions

Advise patients of the risk of cardiovascular adverse reactions, including ventricular fibrillation, myocardial infarction, and cardiogenic shock. Advise patients to contact their healthcare provider immediately to report chest pain and irregular heartbeats. [see Warnings and Precautions (5.7)]

Renal Toxicity

Advise patients of the risk of renal toxicity. Inform patients of the need for healthcare providers to monitor kidney function [see Warnings and Precautions (5.8)].

Bowel Obstruction and Perforation

Advise patients to contact their healthcare provider immediately for signs and symptoms of bowel obstruction and perforation, including severe abdominal pain or repeated vomiting [see Warnings and Precautions (5.9)].

Embryo-Fetal Toxicity

Advise pregnant women of the potential risk to a fetus. Advise femalesof reproductive potential to inform their healthcare provider of a known or suspected pregnancy [see Warnings and Precautions (5.11), Use in Specific Populations (8.1, 8.3)].

Advise females of reproductive potential to use effective contraception during treatment with RITUXAN HYCELA and for 12 months after the last dose of of rituximab-containing products, including RITUXAN HYCELA [see Use in Specific Populations (8.3)].

Lactation

Advise women not to breastfeed during treatment with RITUXAN HYCELA and for 6 months after the last dose [see Use in Specific Populations (8.2)].

RITUXAN HYCELA® [rituximab and hyaluronidase human]

Manufactured by:
Genentech, Inc.
A Member of the Roche Group
1 DNA Way
South San Francisco, CA 94080-4990
US License No.: 1048

RITUXAN HYCELA® is a registered trademark of Biogen.
Jointly marketed by: Biogen and Genentech USA, Inc.
©2021 Biogen and Genentech USA, Inc.

MEDICATION GUIDE
RITUXAN HYCELA® [rih-TUKS-an hye-SELL-uh]
(rituximab and hyaluronidase human)
injection

What is the most important information I should know about RITUXAN HYCELA?
RITUXAN HYCELA can cause serious side effects that can lead to death, including:

- Severe skin and mouth reactions. Tell your healthcare provider or get medical help right away if you get any of these symptoms at any time during your treatment with RITUXAN HYCELA:
  - painful sores or ulcers on your skin, lips or in your mouth
  - blisters
  - peeling skin
  - rash
  - pustules
- Hepatitis B virus (HBV) reactivation. Before you receive RITUXAN HYCELA, your doctor will do blood tests to check for HBV infection. If you have had hepatitis B or are a carrier of hepatitis B virus, receiving RITUXAN HYCELA could cause the virus to become an active infection again. Hepatitis B reactivation may cause serious liver problems including liver failure, and death. Your healthcare provider will monitor you for hepatitis B infection during and for several months after you stop receiving RITUXAN HYCELA.
  Tell your healthcare provider right away if you get worsening tiredness, or yellowing of your skin or white part of your eyes during treatment with RITUXAN HYCELA.
- Progressive Multifocal Leukoencephalopathy (PML). PML is a rare, serious brain infection caused by a virus that can happen in people who receive RITUXAN HYCELA. People with weakened immune systems can get PML. PML can result in death or severe disability. There is no known treatment, prevention, or cure for PML.
  Tell your healthcare provider right away if you have any new or worsening symptoms or if anyone close to you notices these symptoms:
  - confusion
  - dizziness or loss of balance
  - difficulty walking or talking
  - decreased strength or weakness on one side of your body
  - vision problems, such as blurred vision or loss of vision
- Serious allergic reactions and other severe reactions.
  Serious allergic reactions, and reactions due to release of certain substances by your body that can lead to death, can happen with rituximab products, including RITUXAN HYCELA.
  Skin reactions at or near the injection site (local), including injection site reactions, can happen with RITUXAN HYCELA. Symptoms at or near the injection site may include: pain, swelling, hardness, redness, bleeding, itching, and rash. These reactions sometimes happen more than 24 hours after an injection of RITUXAN HYCELA.
  Tell your healthcare provider or get medical help right away if you get any of these symptoms during or after an injection of RITUXAN HYCELA:

- hives (red itchy welts) or rash
- itching
- swelling of your lips, tongue, throat or face
- sudden cough
- shortness of breath, difficulty breathing, or wheezing
- weakness

- dizziness or feel faint
- palpitations (feel like your heart is racing or fluttering)
- chest pain
- fever
- chills or shaking chills

See "What are the possible side effects of RITUXAN HYCELA?" for more information about side effects.

What is RITUXAN HYCELA?
RITUXAN HYCELA is a prescription medicine used to treat adults with:

- Follicular Lymphoma (FL): alone or with certain chemotherapy medicines.
- Diffuse Large B-Cell Lymphoma (DLBCL): with certain other chemotherapy medicines in people who have not had previous treatment for their DLBCL.
- Chronic Lymphocytic Leukemia (CLL): with the chemotherapy medicines fludarabine and cyclophosphamide.

You can only receive RITUXAN HYCELA after you receive at least 1 full dose of a rituximab product by IV infusion. Read the rituximab by IV infusion Medication Guide for more information about severe infusion reactions, which usually happen during the first dose with a rituximab product given by IV infusion.
RITUXAN HYCELA is not for use to treat medical conditions other than cancers.
It is not known if RITUXAN HYCELA is safe and effective in children.

Before you receive RITUXAN HYCELA, tell your healthcare provider about all of your medical conditions, including if you:

- have had a severe reaction to a rituximab product or RITUXAN HYCELA
- have a history of heart problems, irregular heart beat or chest pain
- have lung or kidney problems
- have an infection or weakened immune system
- have or have had any severe infections including:
  - Hepatitis B virus (HBV)
  - Hepatitis C virus (HCV)
  - Cytomegalovirus (CMV)
  - Herpes simplex virus (HSV)
  - Parvovirus B19
  - Varicella zoster virus (chickenpox or shingles)
  - West Nile Virus
- have had a recent vaccination or are scheduled to receive vaccinations. You should not receive certain vaccines before or during treatment with RITUXAN HYCELA.
- are pregnant or plan to become pregnant. RITUXAN HYCELA may harm your unborn baby.
  Females who are able to become pregnant:
  - Your healthcare provider should check to see if you are pregnant before you receive RITUXAN HYCELA.
  - You should use effective birth control (contraception) during treatment with RITUXAN HYCELA and for 12 months after the last dose of RITUXAN HYCELA. Talk to your healthcare provider about effective birth control.
  - Tell your healthcare provider if you become pregnant or think you may be pregnant during treatment with RITUXAN HYCELA.
- are breastfeeding or plan to breastfeed. RITUXAN HYCELA may pass into your breast milk. Do not breastfeed during treatment and for 6 months after your last dose of RITUXAN HYCELA.

Tell your healthcare provider about all the medicines you take, including prescription and over-the-counter medicines, vitamins, and herbal supplements.

How will I receive RITUXAN HYCELA?

- RITUXAN HYCELA is given as an injection under the skin, in the stomach-area (abdomen).
- RITUXAN HYCELA is injected over 5 or 7 minutes.
- Your healthcare provider will prescribe medicines before the injection of RITUXAN HYCELA to help reduce side effects such as fever and chills.
- Your healthcare provider should monitor you for side effects for at least 15 minutes after you receive an injection of RITUXAN HYCELA.
- If you have CLL, your healthcare provider should prescribe medicines to help prevent certain infections during treatment and for up to 12 months following treatment with RITUXAN HYCELA.

Before each injection of RITUXAN HYCELA treatment, your healthcare provider or nurse will ask you questions about your general health. Tell your healthcare provider or nurse about any new symptoms.

What are possible side effects of RITUXAN HYCELA?
RITUXAN HYCELA can cause serious side effects, including:

- See "What is the most important information I should know about RITUXAN HYCELA?"
- Tumor Lysis Syndrome (TLS). TLS is caused by the fast breakdown of cancer cells. TLS can cause you to have:
  - kidney failure and the need for dialysis treatment
  - abnormal heart rhythm
  TLS can happen within 12 to 24 hours after an injection of RITUXAN HYCELA. Your healthcare provider may do blood tests to check you for TLS. Your healthcare provider may give you medicine to help prevent TLS.
  Tell your healthcare provider right away if you have any of the following signs or symptoms of TLS:

- nausea
- vomiting

- diarrhea
- lack of energy

- Serious infections. Serious infections can happen during and after treatment with RITUXAN HYCELA, and can lead to death. Rituximab products can increase your risk of getting infections and can lower the ability of your immune system to fight infections. Types of serious infections that can happen with RITUXAN HYCELA include bacterial, fungal, and viral infections. After receiving RITUXAN HYCELA, some people have developed low levels of certain antibodies in their blood for a long period of time (longer than 11 months). Some of these people with low antibody levels developed infections. Tell your healthcare provider right away if you have any symptoms of infection:
  - fever
  - cold symptoms, such as runny nose or sore throat that do not go away
  - flu symptoms, such as cough, tiredness, and body aches
  - earache or headache
  - pain during urination
  - white patches in the mouth or throat
  - cuts, scrapes or incisions that are red, warm, swollen or painful
- Heart problems. RITUXAN HYCELA may cause chest pain, irregular heartbeats, and heart attack. Your healthcare provider may monitor your heart during and after treatment with RITUXAN HYCELA if you have symptoms of heart problems or have a history of heart problems. Tell your healthcare provider right away if you have chest pain or irregular heartbeats during treatment with RITUXAN HYCELA.
- Kidney problems RITUXAN HYCELA can cause severe kidney problems that can lead to death. Your healthcare provider should do blood tests to check how well your kidneys are working.
- Stomach and serious bowel problems that can sometimes lead to death. Bowel problems, including blockage or tears in the bowel, can happen if you receive RITUXAN HYCELA with chemotherapy medicines. Tell your healthcare provider right away if you have severe stomach-area (abdomen) pain or repeated vomiting during treatment with RITUXAN HYCELA.

Your healthcare provider will stop treatment with RITUXAN HYCELA if you have severe, serious or life-threatening side effects.
The most common side effects of RITUXAN HYCELA in people with Follicular Lymphoma (FL) include: infections, low white blood cell count, nausea, constipation, cough, and tiredness.
The most common side effects of RITUXAN HYCELA in people with Diffuse Large B-cell Lymphoma (DLBCL) include: infections, low white blood cell count, loss of hair, nausea, and low red blood cell count.
The most common side effects of RITUXAN HYCELA in people with Chronic Lymphocytic Leukemia (CLL) include: infections, low white blood cell count, nausea, low platelet count, fever, vomiting, and injection site redness.
These are not all of the possible side effects with RITUXAN HYCELA.
Call your doctor for medical advice about side effects. You may report side effects to FDA at 1-800-FDA-1088.

General information about the safe and effective use of RITUXAN HYCELA.
Medicines are sometimes prescribed for purposes other than those listed in a Medication Guide. You can ask your pharmacist or healthcare provider for information about RITUXAN HYCELA that is written for health professionals.

What are the ingredients in RITUXAN HYCELA?
Active ingredient: rituximab and hyaluronidase human.
Inactive ingredients: L-histidine, L-histidine hydrochloride monohydrate, L-methionine, polysorbate 80, α,α-trehalose dihydrate, and Water for Injection.
Manufactured by: Genentech, Inc., A Member of the Roche Group, 1 DNA Way, South San Francisco, CA 94080-4990
U.S. License No.: 1048
Jointly marketed by: Biogen and Genentech USA, Inc.
RITUXAN HYCELA® is a registered trademark of Biogen.
©2021 Biogen and Genentech USA, Inc.
For more information, go to www.RITUXANHYCELA.com or call 1-877-436-3683.

This Medication Guide has been approved by the U.S. Food and Drug Administration

Revised: 6/2021

Representative sample of labeling (see the HOW SUPPLIED section for complete listing):

PRINCIPAL DISPLAY PANEL - 11.7 mL Vial Carton

Rx only

NDC 50242-108-01

Rituxan Hycela®
(rituximab and
hyaluronidase human)
Injection

1,400 mg and
23,400 Units/11.7 mL
(120 mg and 2,000 Units/mL)

For Subcutaneous Use Only.
Give the subcutaneous
injection over 5 to 7 minutes.

Single-Dose Vial.
Discard Unused Portion.

Attention Pharmacist: Dispense the
accompanying Medication Guide to
each patient.

1 vial

Genentech | Biogen®

10214985

PRINCIPAL DISPLAY PANEL - 13.4 mL Vial Carton

Rx only

NDC 50242-109-01

Rituxan Hycela®
(rituximab and
hyaluronidase human)
Injection

1,600 mg and
26,800 Units/13.4 mL
(120 mg and 2,000 Units/mL)

For Subcutaneous Use Only.
Give the subcutaneous
injection over 5 to 7 minutes.

Single-Dose Vial.
Discard Unused Portion.

Attention Pharmacist: Dispense the
accompanying Medication Guide to
each patient.

1 vial

Genentech | Biogen®

10214988